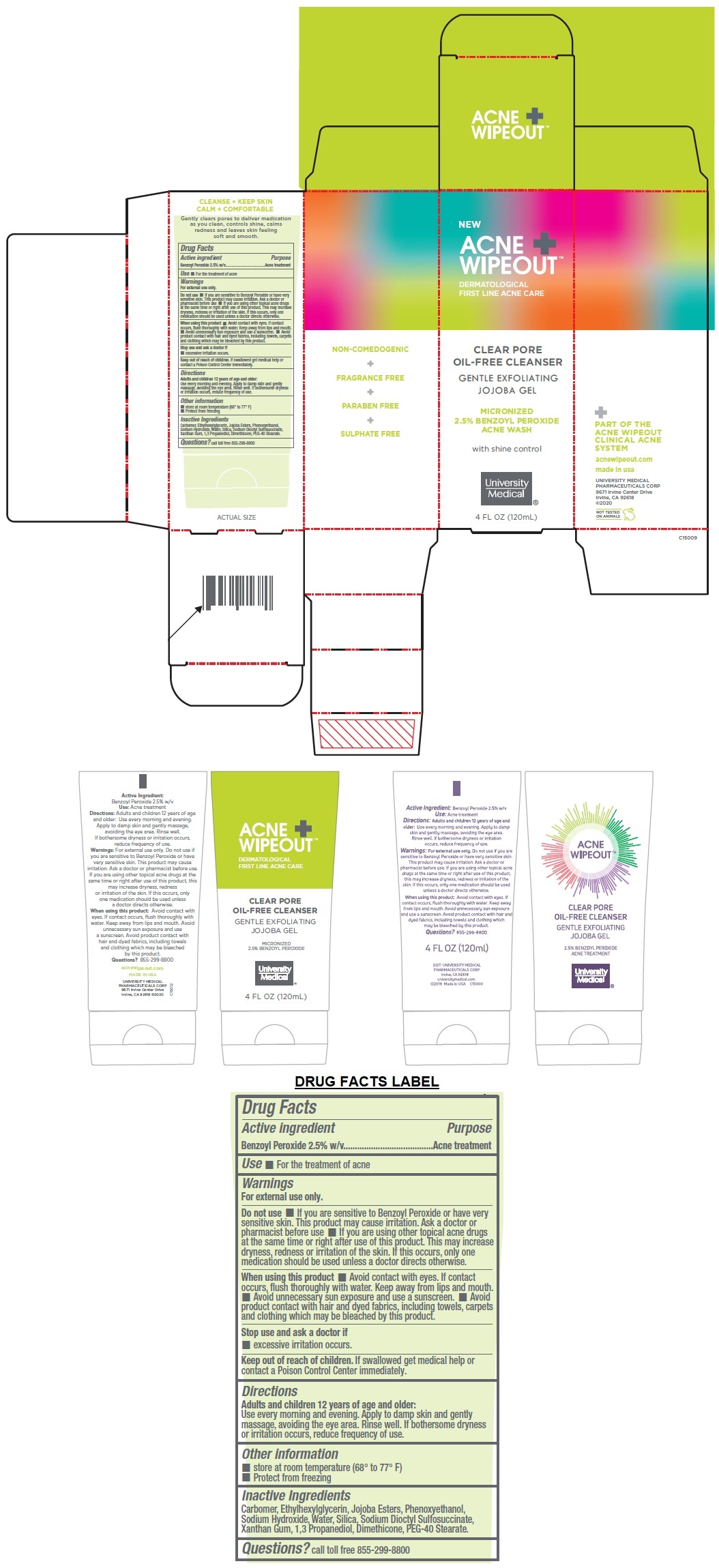 DRUG LABEL: ACNE WIPEOUT CLEAR PORE oil-FREE CLEANSER
NDC: 50544-151 | Form: GEL
Manufacturer: University Medical Pharmaceuticals Corp.
Category: otc | Type: HUMAN OTC DRUG LABEL
Date: 20201002

ACTIVE INGREDIENTS: BENZOYL PEROXIDE 2.5 g/100 mL
INACTIVE INGREDIENTS: CARBOMER HOMOPOLYMER, UNSPECIFIED TYPE; ETHYLHEXYLGLYCERIN; JOJOBA OIL; PHENOXYETHANOL; SODIUM HYDROXIDE; WATER; SILICON DIOXIDE; DOCUSATE SODIUM; XANTHAN GUM; PROPANEDIOL; DIMETHICONE; PEG-40 STEARATE

ACNE WIPEOUT™ CLEAR PORE OIL-FREE CLEANSER

Active ingredient

Benzoyl Peroxide 2.5% w/v

Purpose

Acne treatment

Use

• For the treatment of acne

Warnings

For external use only.

Do not use • If you are sensitive to Benzoyl Peroxide or have very sensitive skin. This product may cause irritation. Ask a doctor or pharmacist before use • If you are using other topical acne drugs at the same time or right after use of this product. This may increase dryness, redness or irritation of the skin. If this occurs, only one medication should be used unless a doctor directs otherwise.

When using this product • Avoid contact with eyes. If contact occurs, flush thoroughly with water. Keep away from lips and mouth. • Avoid unnecessary sun exposure and use a sunscreen. • Avoid product contact with hair and dyed fabrics, including towels, carpets and clothing which may be bleached by this product.

Stop use and ask a doctor if
• excessive irritation occurs.

Keep out of reach of children. If swallowed get medical help or contact a Poison Control Center immediately.

Directions

Adults and children 12 years of age and older:
Use every morning and evening. Apply to damp skin and gently massage, avoiding the eye area. Rinse well. If bothersome dryness or irritation occurs, reduce frequency of use.

Other information

• store at room temperature (68° to 77° F)
• Protect from freezing

Inactive Ingredients

Carbomer, Ethylhexylglycerin, Jojoba Esters, Phenoxyethanol, Sodium Hydroxide, Water, Silica, Sodium Dioctyl Sulfosuccinate, Xanthan Gum, 1,3 Propanediol, Dimethicone, PEG-40 Stearate.

Questions? call toll free 855-299-8800

DERMATOLOGICAL FIRST LINE ACNE CARE

GENTLE EXFOLIATING JOJOBA GEL

MICRONIZED 2.5% BENZOYL PEROXIDE ACNE WASH

with shine control

PART OF THE ACNE WIPEOUT CLINICAL ACNE SYSTEM

acnewipeout.com

made in usa

UNIVERSITY MEDICAL

PHARMACEUTICALS CORP

9671 Irvine Center Drive

Irvine, CA 92618

©2020

NOT TESTED ON ANIMALS

NON-COMEDOGENIC + FRAGRANCE FREE + PARABEN FREE + SULPHATE FREE

CLEANSE + KEEP SKIN

CALM + COMFORTABLE

Gently clears pores to deliver medication as you clean, controls shine, calms redness and leaves skin feeling soft and smooth.